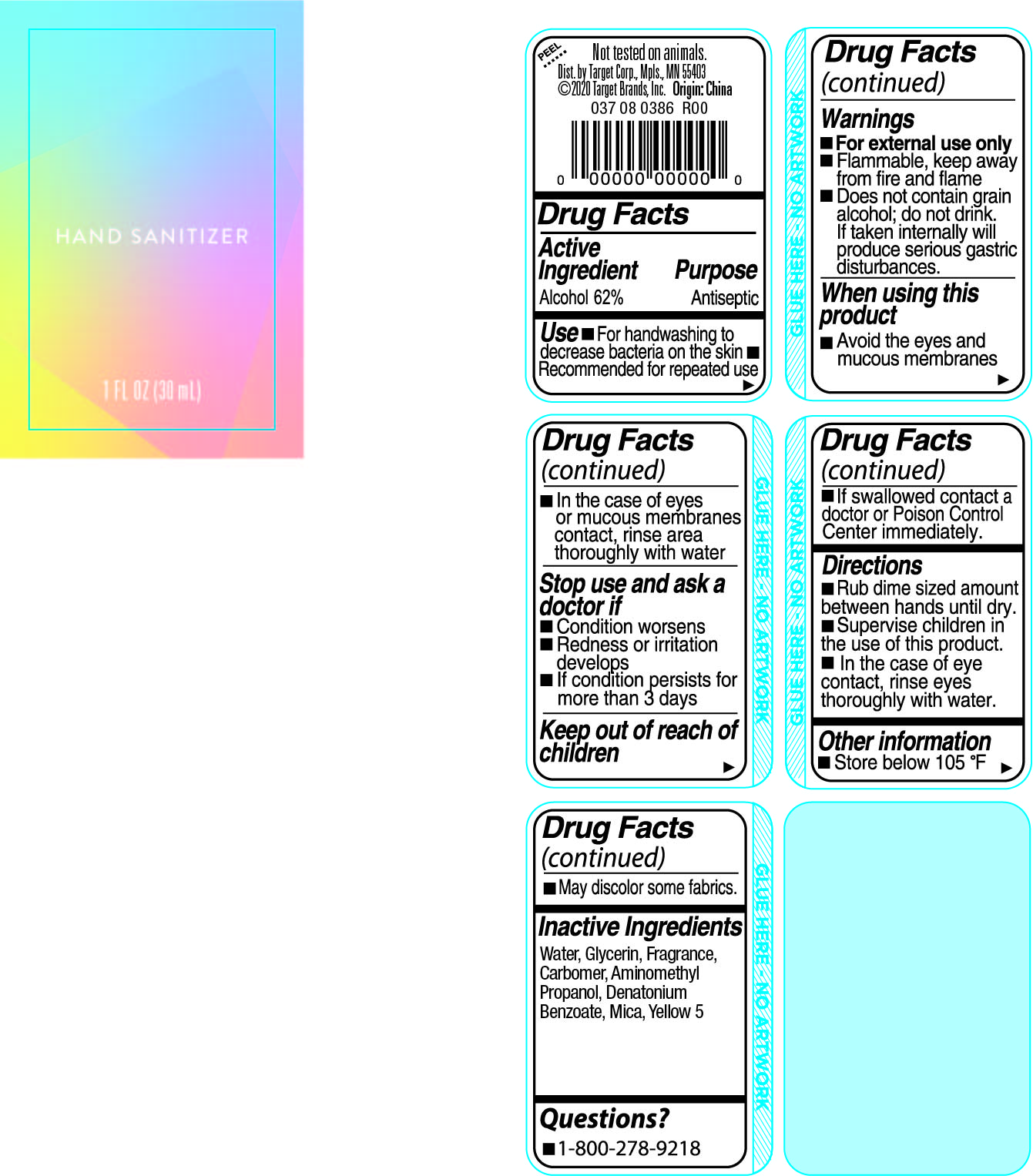 DRUG LABEL: Hand Sanitizer
NDC: 61805-401 | Form: GEL
Manufacturer: Bath Concept Cosmetics (Dongguan) Co., Ltd
Category: otc | Type: HUMAN OTC DRUG LABEL
Date: 20200707

ACTIVE INGREDIENTS: ALCOHOL 62 mL/100 mL
INACTIVE INGREDIENTS: MICA; GLYCERIN; CARBOMER HOMOPOLYMER, UNSPECIFIED TYPE; WATER; DENATONIUM BENZOATE; AMINOMETHYLPROPANOL; FD&C YELLOW NO. 5

BthCncptsTrget Gold Hnd Sntzr

Active Ingredient

Alcohol 62%

Purpose

Antiseptic

Use

■ For handwashing to decrease bacteria on the skin ■ Recommended for repeated use

Warnings

■ For external use only

■ Flammable, keep away from fire & flame

■ Does not contain grain alcohol;do not drink. If taken internally will produce serious gastric disturbances

When using this product

■ Avoid the eyes and mucous membranes

■ In the case of eyes or mucous membranes contact, rinse area thoroughly with water

Stop use and ask a doctor if

■ Condition worsens

■ Redness or irritation develops

■ If condition persists for more than 3 days

Keep out of reach of children

■ If swallowed contact a doctor or Poison Control Center immediately.

Directions

■ Rub dime sized amount between hands until dry

■ Supervise children in the use of this product

■ In the case of eye contact, rinse eyes thoroughly with water

Other information

■ Store below 105°F ■ May discolor some fabrics

Inactive Ingredients

Water, Glycerin, Fragrance, Carbomer, Aminomethyl Propanol, Denatonium Benzoate, Mica, Yellow 5

Questions?

■ 1-800-278-9218